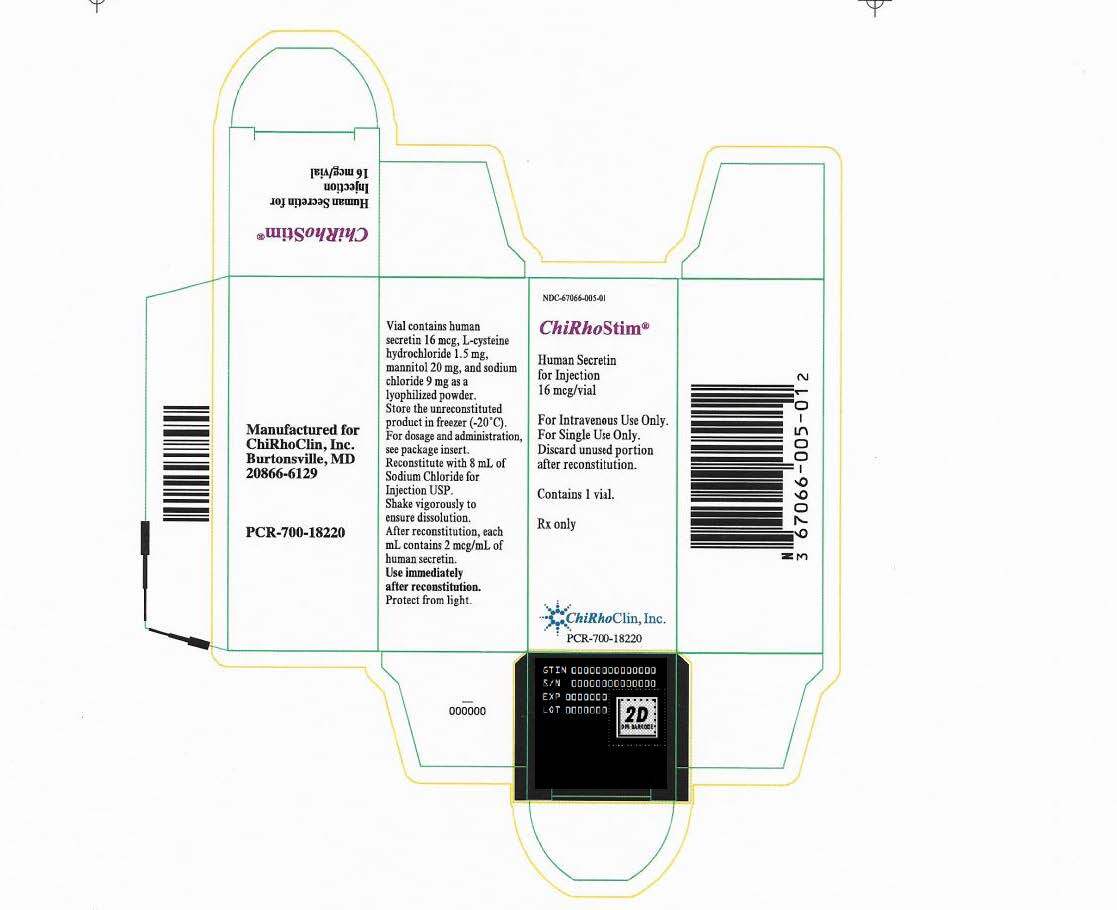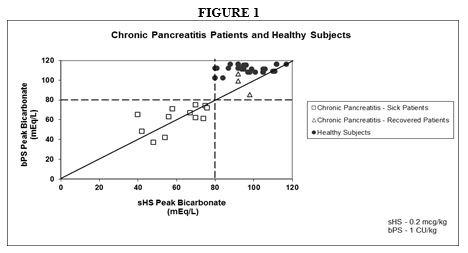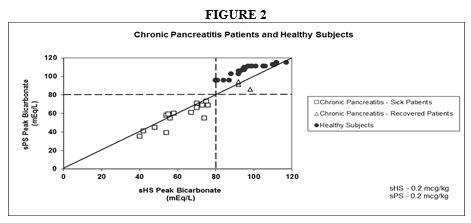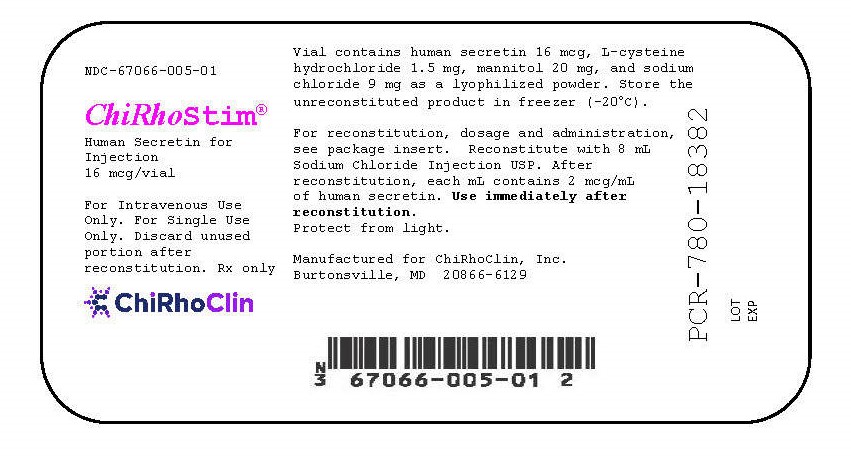 DRUG LABEL: ChiRhoStim
NDC: 67066-005 | Form: INJECTION, POWDER, LYOPHILIZED, FOR SOLUTION
Manufacturer: ChiRhoClin, Inc.
Category: prescription | Type: HUMAN PRESCRIPTION DRUG LABEL
Date: 20251008

ACTIVE INGREDIENTS: SECRETIN HUMAN 16 ug/8 mL

HIGHLIGHTS OF PRESCRIBING INFORMATION

These highlights do not include all the information needed to use CHIRHOSTIM® safely and effectively. See full prescribing information for CHIRHOSTIM®.
CHIRHOSTIM® (human secretin) for injection, for intravenous use
Initial U.S. Approval: 2004

INDICATIONS AND USAGE

- ChiRhoStim® is a secretin class hormone indicated for stimulation of:
- pancreatic secretions, including bicarbonate, to aid in the diagnosis of exocrine pancreas dysfunction (1)
- gastrin secretion to aid in the diagnosis of gastrinoma (1)
- pancreatic secretions to facilitate the identification of the ampulla of Vater and the accessory papilla during endoscopic retrograde cholangiopancreatography (ERCP) (1)

DOSAGE AND ADMINISTRATION

- To avoid an incorrect stimulation test result, discontinue the following drugs for the recommended amount of time prior to administration of ChiRhoStim®:

- anticholinergic drugs: at least 5 half-lives. (2.1, 5.1, 7.1)
- H2-receptor antagonists: at least 2 days. (2.1, 5.2, 7.2)
- proton pump inhibitors (PPIs): consult the prescribing information for specific PPIs. (2.1, 5.2, 7.2)

- The recommended dosage by indication is shown in the table:

Indication | Recommended Dosage Regimen (2.2)
Stimulation of pancreatic secretions, including bicarbonate, to aid in the diagnosis of exocrine pancreas dysfunction | 0.2 mcg/kg by intravenous injection over 1 minute
Stimulation of gastrin secretion to aid in diagnosis of gastrinoma | 0.4 mcg/kg by intravenous injection over 1 minute
Stimulation of pancreatic secretions to facilitate the identification of the ampulla of Vater and accessory papilla during endoscopic retrograde cholangiopancreatography (ERCP) | 0.2 mcg/kg by intravenous injection over 1 minute

- Determine the number of vials to be reconstituted based on the patient’s weight and prescribed dose (2.2)
- ChiRhoStim® must be reconstituted with 0.9% Sodium Chloride Injection prior to administration (2.2)
- See full prescribing information for complete information on exocrine test methods (2.3)

DOSAGE FORMS AND STRENGTHS

For injection: 16 mcg or 40 mcg of human secretin as a lyophilized powder in single-dose vial for reconstitution (3)

CONTRAINDICATIONS

None (4)

WARNINGS AND PRECAUTIONS

- Hyporesponse to Secretin Stimulation Testing in Patients with Vagotomy, Inflammatory Bowel Disease or Receiving Anticholinergics: Discontinue anticholinergic drugs at least 5 half-lives prior to stimulation testing; consider additional testing and clinical assessments for aid in diagnosis. (2.1, 5.1, 7.1)
- Hyperresponse to Secretin Stimulation Testing: Increased gastrin secretion in patients receiving H2-receptor antagonists or PPIs falsely suggesting gastrinoma; discontinue co-administered drug prior to stimulation testing. Increased pancreatic secretions in patients with alcoholic or other liver disease masking coexisting pancreatic disease; consider additional testing and clinical assessments for aid in diagnosis. (2.1, 5.2, 7.2)

ADVERSE REACTIONS

Most common adverse reactions (≥2 patients) are nausea, vomiting, flushing, and upset stomach. (6.1)

To report SUSPECTED ADVERSE REACTIONS, contact ChiRhoClin, Inc. at 1-877-272-4888 or FDA at 1-800-FDA-1088 or www.fda.gov/medwatch.

See 17 for PATIENT COUNSELING INFORMATION.

Revised: 07/2017

FULL PRESCRIBING INFORMATION

INDICATIONS AND USAGE

ChiRhoStim® is indicated for the stimulation of:

- pancreatic secretions, including bicarbonate, to aid in the diagnosis of pancreatic exocrine dysfunction.
- gastrin secretion to aid in the diagnosis of gastrinoma, and
- pancreatic secretions to facilitate the identification of the ampulla of Vater and accessory papilla during endoscopic retrograde cholangiopancreatography (ERCP).

DOSAGE AND ADMINISTRATION

2.2 Preparation and Dosage Regimen

The recommended dosage regimen of ChiRhoStim® by indication is shown below in Table 1.

TABLE 1: Dosage by Indication

Indication | Recommended Dosage Regimen
Stimulation of pancreatic secretions, including bicarbonate, to aid in the diagnosis of exocrine pancreas dysfunction | 0.2 mcg/kg by intravenous injection over 1 minute
Stimulation of gastrin secretion to aid in diagnosis of gastrinoma | 0.4 mcg/kg by intravenous injection over 1 minute
Stimulation of pancreatic secretions to facilitate the identification of the ampulla of Vater and accessory papilla during endoscopic retrograde cholangiopancreatography (ERCP) | 0.2 mcg/kg by intravenous injection over 1 minute

Preparation of Recommended Dosage

- ChiRhoStim® is a lyophilized powder, which requires reconstitution prior to intravenous administration.
- Determine the number of vials needed for the prescribed dosage based on the patient’s weight and recommended dosage. Follow these steps to determine the patient dose:
  - Total dose (mcg) = patient’s weight (kg) x prescribed dose (mcg/kg).
  - Total injection volume (mL) = total dose (mcg) divided by the concentration of the reconstituted solution (2 mcg/mL).
  - Round the total injection volume to the nearest tenth of a mL.
  - Total number of vials = total injection volume divided by the vial volume (8 mL).

- To reconstitute one 16 mcg vial:

- Dissolve the contents of the ChiRhoStim® 16 mcg vial in 8 mL of 0.9% Sodium Chloride Injection, USP, to yield a concentration of 2 mcg/mL.
- Shake vigorously to ensure dissolution.
- Inspect the reconstituted solution visually for particulate matter and discoloration prior to administration. If particulate matter or discoloration is seen, discard the reconstituted solution.

- To reconstitute one 40 mcg vial:

- Dissolve the contents of the ChiRhoStim® 40 mcg vial in 10 mL of 0.9% Sodium Chloride Injection, USP, to yield a concentration of 4 mcg/mL.
- Shake vigorously to ensure dissolution.
- Inspect the reconstituted solution visually for particulate matter and discoloration prior to administration. If particulate matter or discoloration is seen, discard the reconstituted solution.

- Repeat steps above to reconstitute additional vials, as needed, to administer the total dose.
- Use immediately after reconstitution and discard any unused portion.

2.3 Administration and Test Methods

Stimulation testing with ChiRhoStim® should only be performed by physicians with sufficient expertise. Ensure that the institution has established normative ranges for pancreatic exocrine response.

Stimulation of Pancreatic Secretions, including Bicarbonate, to Aid in the Diagnosis of Exocrine Pancreas Dysfunction:

Preparation:

- Instruct patients to fast for at least 12 to 15 hours prior to beginning the test.

Sample Collection: [performed using either the gastroduodenal/Dreiling tube (fluoroscopic) or endoscopic collection method]

- Gastroduodenal (Dreiling) Tube Collection Method
  - Pass a radiopaque, double-lumen gastroduodenal tube through the mouth using a guidewire.
  - Under fluoroscopic guidance, place the opening of the proximal lumen in the gastric antrum and the opening of the distal lumen beyond the ampulla of Vater. Confirm the tube positioning and secure the tube.
  - Connect both the proximal (gastric) and distal (duodenal) lumens to low intermittent suction, and apply negative pressure of 25 to 40 mmHg to both lumens.
  - Collect a sample of the duodenal contents and check the pH of the aspirate to verify tube position. Proceed to next step if the duodenal aspirate has a pH of 6 or higher. If the pH is less than 6, reposition the tube.
  - Collect a baseline sample of duodenal fluid for a 15-minute period.
  - Administer ChiRhoStim® at a dose of 0.2 mcg/kg body weight intravenously over 1 minute [see Dosage and Administration (2.2)]. For the 60-minute period following the injection, collect four consecutive 15-minute samples of duodenal fluid. Clear the duodenal lumen of the tube with an injection of air after each 15-minute sample collection. Note that wide variation in aspirate volumes is indicative of incomplete aspiration between samples.

- Endoscopic Collection Method: Endoscopic Pancreatic Function Test (ePFT)

- Administer a topical anesthetic spray to the posterior pharynx and place a bite block in the mouth.
- Perform a standard upper endoscopy by passing the endoscope into the stomach with the patient in the left lateral decubitus position.
  - After gastric insufflation, aspirate all gastric fluid through the endoscope and discard.
  - Pass the endoscope through the pylorus into small intestine and position the tip of the endoscope at the junction of the second and third portion of the duodenum.
  - Aspirate duodenal fluid for several seconds to clear the residual gastric acid from the tube.
  - Collect a baseline aspirate of duodenal fluid (3 to 5 mL) from the post-bulbar duodenum.
  - Administer ChiRhoStim® at a dose of 0.2 mcg/kg of body weight intravenously over 1 minute [see Dosage and Administration (2.2)].
  - Starting 15 minutes after administration of ChiRhoStim®, collect 4 timed duodenal fluid aspirates (each 3 to 5 mL) at 15-minute intervals. Keep the patient in the left lateral decubitus position throughout the procedure.

Sample Handling and Interpretation:

- Place fluid specimens on ice for immediate measurement of bicarbonate concentration. If samples will not be analyzed immediately, store fluid at –80°C.
- Peak bicarbonate concentrations of 80 to 130 mEq/L after administration indicate normal pancreatic exocrine function.

Stimulation of Gastrin Secretion to Aid in the Diagnosis of Gastrinoma:

Preparation:

- Instruct patients to fast for at least 12 hours prior to beginning the test.

Sample Collection:

- Before administering ChiRhoStim®, draw two blood samples for determination of fasting serum gastrin levels (baseline values).
- Administer ChiRhoStim® at a dose of 0.4 mcg/kg of body weight intravenously over 1 minute [see Dosage and Administration (2.2)].

- Collect post-injection blood samples after 1, 2, 5, 10, and 30 minutes for determination of serum gastrin concentrations.

Sample Interpretation:

- Gastrinoma is strongly suspected in patients who show an increase in serum gastrin concentration of more than 110 picograms (pg) per mL over baseline levels on any of the post injection samples.

Stimulation of Pancreatic Secretions to Facilitate the Identification of the Ampulla of Vater and Accessory Papilla During Endoscopic Retrograde Cholangiopancreatography (ERCP):

When difficulty is encountered by the endoscopist in identifying the ampulla of Vater or in identifying the accessory papilla in patients with pancreas divisum:

- Administer ChiRhoStim® at a dose of 0.2 mcg/kg of body weight intravenously over 1 minute [see Dosage and Administration (2.2)].
- Visible excretion of pancreatic fluid from the orifices of these papillae will enable their identification and facilitate cannulation.

DOSAGE FORMS AND STRENGTHS

For injection: 16 mcg or 40 mcg of human secretin as a white lyophilized powder in single-dose vial for reconstitution.

CONTRAINDICATIONS

None.

WARNINGS AND PRECAUTIONS

Patients with alcoholic or other liver disease may be hyperresponsive to stimulation with ChiRhoStim®, masking the presence of coexisting pancreatic disease. Consider additional testing and clinical assessments for aid in diagnosis.

ADVERSE REACTIONS

6.1 Clinical Trials Experience

Because clinical trials are conducted under varying conditions, adverse reaction rates observed during the clinical trials of a drug cannot always be directly compared to the rates observed during the clinical trials of another drug and may not reflect the adverse reaction rates observed in practice.

The data described below reflect exposure to ChiRhoStim® in 531 patients from an open-label clinical trial. The population consisted of patients aged 1 to 91 years, 185 males, 346 females, 480 Caucasians, 31 Blacks, 12 American Indians, 6 Hispanics, and 2 Asians with known or suspected diseases of the exocrine pancreas including chronic pancreatitis and pancreatic cancer. Most patients received a single dose of ChiRhoStim® in a dose range of 0.2 mcg/kg to 0.4 mcg/kg. The most common adverse reactions (reported in at least 2 patients in the trial) are listed in Table 2.

TABLE 2

Adverse Reactions in at Least 2 Patients Treated with a Single-Dose of ChiRhoStim® in a Clinical Trial

Adverse Reaction | ChiRhoStim®; Number of Patients; N = 531
Nausea | 9
Vomiting | 3
Flushing | 2
Upset stomach | 2

DRUG INTERACTIONS

7.1 Hyporesponse with Anticholinergics

The concomitant use anticholinergic drugs may cause a hyporesponse to stimulation testing with ChiRhoStim®. Discontinue anticholinergic drugs at least 5 half-lives before administering ChiRhoStim® [see Dosage and Administration (2.1)].

7.2 Hyperresponse of Gastrin Secretion with H2-Receptor Antagonists and PPIs

The concomitant use of H2-receptor antagonists or PPIs may cause a hyperresponse in gastrin secretion in response to stimulation testing with ChiRhoStim®, falsely suggesting gastrinoma.

Discontinue H2-receptor antagonists at least 2 days before administering ChiRhoStim® to aid in the diagnosis of gastrinoma.

The time it takes for serum gastrin concentrations to return to baseline following discontinuation of PPIs is specific to the individual drug. Consult the prescribing information of each specific PPI before administering ChiRhoStim® to aid in the diagnosis of gastrinoma.

USE IN SPECIFIC POPULATIONS

8.1 Pregnancy

Risk Summary

There are no available data (either clinical studies or postmarketing reports) of use of synthetic human secretin in pregnant women. Animal reproduction studies have not been conducted with synthetic human secretin.

The estimated background risk of major birth defects and miscarriage for the indicated populations are unknown. All pregnancies have a background risk of birth defect, loss, or other adverse outcomes. In the U.S. general population, the estimated background risk of major birth defects and miscarriage in clinically recognized pregnancies is 2% to 4% and 15% to 20%, respectively.

8.2 Lactation

Risk Summary

There are no data on the presence of synthetic human secretin in human or animal milk, the effects of synthetic human secretin on the breastfed infant, or the effects of synthetic human secretin on milk production. The developmental and health benefits of breastfeeding should be considered along with the mother’s clinical need for ChiRhoStim® and any potential adverse effects on the breastfed infant from ChiRhoStim® or from the underlying maternal condition.

8.4 Pediatric Use

The safety and effectiveness of ChiRhoStim® in pediatric patients have not been established.

8.5 Geriatric Use

Among the 531 patients who have received ChiRhoStim® in a clinical trial, 11% were 65 years of age or older and 5% were 75 years of age or older. No overall differences in safety, pharmacologic response, or diagnostic effectiveness were observed between these subjects and younger subjects, and other reported clinical experience has not identified differences in responses between the elderly and the younger patients, but greater sensitivity of some older individuals cannot be ruled out.

DESCRIPTION

ChiRhoStim® is a pure sterile, nonpyrogenic, lyophilized white cake powder acetate salt of secretin, a peptide hormone. ChiRhoStim® has an amino acid sequence identical to the naturally occurring hormone consisting of 27 amino acids. Synthetic human secretin is chemically defined as follows:

Molecular Weight 3039.44

Empirical Formula: C130H220N44O39

CAS # 108153-74-8

Structural Formula:

His-Ser-Asp-Gly-Thr-Phe-Thr-Ser-Glu-Leu-Ser-Arg-Leu-Arg-Glu-Gly-Ala-Arg-Leu-Gln-Arg-Leu-Leu-Gln-Gly-Leu-Val-NH2

The standard unit of biological activity for ChiRhoStim® is the clinical unit (CU).(2) One (1) CU of secretin biological activity is equal to 0.2 micrograms (mcg) of human secretin.

ChiRhoStim® is available in two strengths:

As a 10 mL single-dose vial which contains 16 mcg of purified synthetic human secretin, 1.5 mg of L-cysteine hydrochloride, 20 mg of mannitol, and 9 mg of sodium chloride. When reconstituted in 8 mL of Sodium Chloride Injection USP, each mL of solution contains 2 mcg synthetic human secretin for intravenous use. The pH of the reconstituted solution has a range of 3 to 6.5.

As a 10 mL single-dose vial which contains 40 mcg of purified synthetic human secretin, 3.75 mg of L-cysteine hydrochloride, 50 mg of mannitol, and 22.5 mg of sodium chloride per vial. When reconstituted in 10 mL of Sodium Chloride Injection USP, each mL of solution contains 4 mcg synthetic human secretin for intravenous use. The pH of the reconstituted solution has a range of 3 to 6.5.

CLINICAL PHARMACOLOGY

Mechanism of Action

12.1 Mechanism of Action

The primary action of ChiRhoStim® is to stimulate pancreatic ductal cells to secrete pancreas fluid in large volumes that contain bicarbonate.

Secretin is a hormone that is normally released from the duodenum upon exposure of the proximal intestinal lumen to gastric acid, fatty acids and amino acids. Secretin is released from enterochromaffin cells in the intestinal mucosa. Secretin receptors have been identified in the pancreas, stomach, liver, colon and other tissues. When secretin binds to secretin receptors on pancreatic duct cells it opens cystic fibrosis transmembrane conductance regulator (CFTR) channels, leading to secretion of bicarbonate-rich-pancreatic fluid. Secretin may also work through vagal-vagal neural pathways since stimulation of the efferent vagus nerve stimulates bicarbonate secretion and atropine blocks secretin-stimulated pancreatic secretion.

Pharmacokinetics

12.3 Pharmacokinetics

The pharmacokinetic profile for synthetic human secretin was evaluated in 12 healthy subjects following a single-dose of human secretin administered as a 0.4 mcg/kg intravenous bolus. The plasma concentrations of human secretin declined to baseline concentrations within 90 to 120 minutes. The elimination half-life of synthetic human secretin is 45 minutes. The clearance of synthetic human secretin is 580.9 ± 51.3 mL/min and the volume of distribution is 2.7 liters.

CLINICAL STUDIES

14.1 Stimulation of Pancreatic Secretions, Including Bicarbonate to Aid in the Diagnosis of Exocrine Pancreas Dysfunction
ChiRhoStim® administered intravenously stimulates the exocrine pancreas to secrete pancreatic juice, which can assist in the diagnosis of exocrine pancreas dysfunction. Normal ranges for pancreatic secretory response to intravenous secretin in patients with defined pancreatic disease have been shown to vary. One source of variation is related to the inter-investigator differences in operative technique.

In two studies, a total of 18 patients with a documented history of chronic pancreatitis were given 0.2 mcg/kg synthetic human secretin (sHS), 0.2 mcg/kg synthetic porcine secretin (sPS), and 1 CU/kg (equal to 0.2 mcg/kg for biologically derived secretin (bPS)) in a crossover design. The results appear in Figures 1 and 2. In another study, 35 healthy subjects were given sHS at a dose of 0.2 mcg/kg. The results appear in Figures 1 and 2.

FIGURE 1

FIGURE 2

The values obtained for Figures 1 and 2 were performed by investigators skilled in performing secretin stimulation testing and are to be taken only as guidelines. These results should not be generalized to results of secretin stimulation testing conducted in other laboratories. However, a volume response of less than 2 mL/kg/hr, bicarbonate concentration of less than 80 mEq/L, and a bicarbonate output of less than 0.2 mEq/kg/hr are consistent with impaired pancreatic function.

A physician or institution planning to perform secretin stimulation testing as an aid to the diagnosis of pancreatic disease should begin by assessing enough normal subjects (greater than 5) to develop proficiency in proper techniques and to generate normal response ranges for the commonly assessed parameters for pancreatic exocrine response to ChiRhoStim®.

In three crossover studies evaluating 21 different patients with a documented history of chronic pancreatitis, sHS was compared to sPS and bPS at a dose of 0.2 mcg/kg for each drug. All of the patients treated with these drugs had peak bicarbonate concentrations of less than 80 mEq/L.

Pancreatic secretory response to intravenous synthetic human secretin in 35 healthy subjects demonstrated a mean peak bicarbonate concentration of 100 mEq/L and a mean total volume over one hour of 260.7 mL. All 35 subjects had peak bicarbonate concentrations greater than or equal to 80 mEq/L.

14.2 Stimulation of Gastrin Secretion to Aid in the Diagnosis of Gastrinoma

ChiRhoStim® administered intravenously stimulates gastrin release in patients with gastrinoma (Zollinger-Ellison Syndrome), whereas no or only small changes in serum gastrin concentrations occur in healthy subjects and in patients with duodenal ulcer disease. Discriminant analysis was used to establish secretin stimulation testing as an aid in the diagnosis of gastrinoma. An increase from basal levels of greater than or equal to 110 pg/mL was the optimal point separating positive and negative tests. This gastrin response is the basis for the use of secretin as a provocative test in the evaluation of patients in whom gastrinoma is a diagnostic consideration.

In a three way crossover study, 6 patients with tissue confirmed gastrinoma received synthetic human secretin (ChiRhoStim®), synthetic porcine secretin and biologically derived porcine secretin at a dose of 0.4 mcg/kg for each drug. Serum gastrin levels were reported to be greater than 110 pg/mL for all secretin products tested after stimulation. Testing of ChiRhoStim® in 12 healthy subjects demonstrated completely negative results for gastrinoma.

14.3 Stimulation of Pancreatic Secretion to Facilitate Identification of the Ampulla of Vater and the Accessory Papilla During Endoscopic Retrograde Cholangiopancreatography (ERCP)

In a randomized, placebo controlled crossover study in 24 patients with pancreas divisum undergoing ERCP, ChiRhoStim® at a dose of 0.2 mcg/kg resulted in 16 of 24 successful cannulations of the minor duct compared to 2 of 24 for placebo.

REFERENCES

1. Gardner TB, Purich ED and Gordon SR. Pancreatic Duct Compliance After Secretin Stimulation. A Novel Endoscopic Ultrasound Diagnostic Tool for Chronic Pancreatitis. Pancreas. 2012 Mar;41(2):290-94.
2. Jorpes, E. and Mutt V. On the biological assay of secretin. The reference standard. Acta Physiol Scand. 1966 Mar;66(3):316-25.

HOW SUPPLIED/STORAGE AND HANDLING

ChiRhoStim® (human secretin), for injection is supplied as a white lyophilized sterile powder in a single-dose vial for reconstitution:

NDC # 67066-005-01 16 mcg

NDC # 67066-007-01 40 mcg

Store at -20°C (freezer). Protect from light.

PATIENT COUNSELING INFORMATION

Advise the patient to tell their healthcare provider all the medications they are taking, including anticholinergic drugs, H2-receptor antagonists or PPIs [see Warnings and Precautions (5.1, 5.2)].

Manufactured for:

ChiRhoClin, Inc.

Burtonsville, MD 20866-6129

005PI508